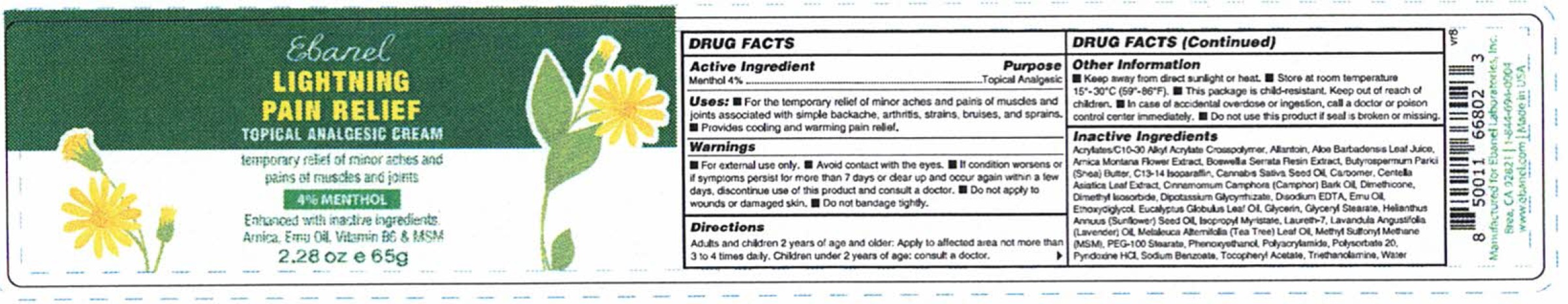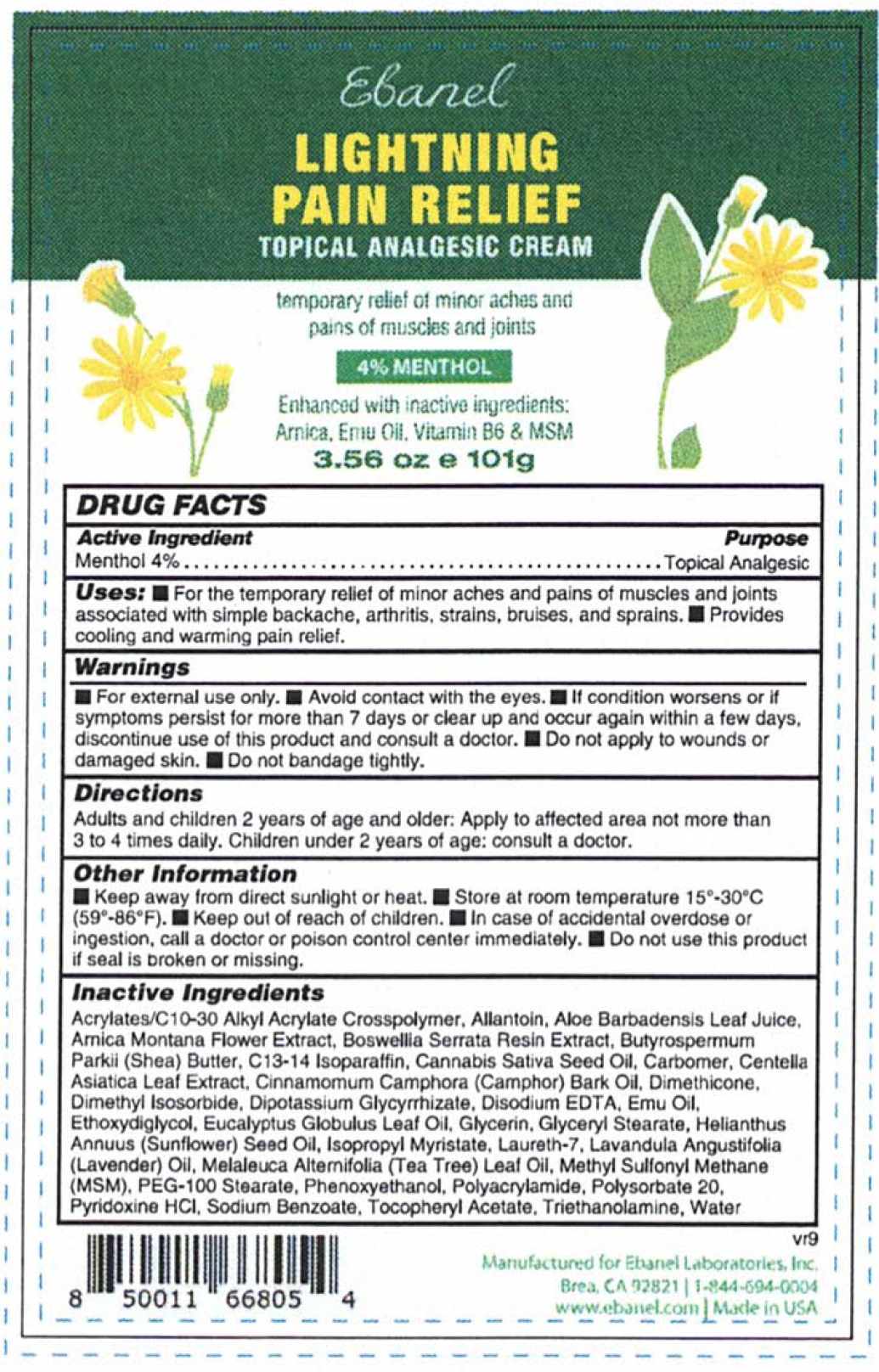 DRUG LABEL: Lightning Pain Relief
NDC: 63742-013 | Form: CREAM
Manufacturer: Clinical Resolution Laboratory, Inc.
Category: otc | Type: HUMAN OTC DRUG LABEL
Date: 20240102

ACTIVE INGREDIENTS: MENTHOL 40 mg/1 g
INACTIVE INGREDIENTS: ALLANTOIN; ALOE VERA LEAF; ARNICA MONTANA FLOWER; INDIAN FRANKINCENSE; SHEA BUTTER; C13-14 ISOPARAFFIN; CANNABIS SATIVA SEED OIL; CARBOMER HOMOPOLYMER, UNSPECIFIED TYPE; CENTELLA ASIATICA LEAF; CAMPHOR OIL; DIMETHICONE; DIMETHYL ISOSORBIDE; GLYCYRRHIZINATE DIPOTASSIUM; EDETATE DISODIUM ANHYDROUS; EMU OIL; DIETHYLENE GLYCOL MONOETHYL ETHER; EUCALYPTUS OIL; GLYCERIN; GLYCERYL MONOSTEARATE; SUNFLOWER OIL; ISOPROPYL MYRISTATE; LAURETH-7; LAVENDER OIL; TEA TREE OIL; PEG-100 STEARATE; PHENOXYETHANOL; POLYSORBATE 20; PYRIDOXINE HYDROCHLORIDE; SODIUM BENZOATE; .ALPHA.-TOCOPHEROL ACETATE; TROLAMINE; WATER

Lightning Pain Relief Cream

Active Ingredient

Menthol 4%

Purpose

Topical Analgesic

Uses:

- For the temporary relief of minor aches and pains of muscles and joints associated with simple backache, arthritis, strains, bruises, and sprains.
- Provides cooling and warming pain relief.

Warnings

- For external use only.
- Avoid contact with the eyes.
- If condition worsens or if symptoms persist for more than 7 days or clear up and occur again within a few days, discontinue use of this product and consult a doctor.
- Do not apply to wounds or damaged skin.
- Do not bandage tightly.

Keep out of reach od children.

- In case of accidental overdose or ingestion, call a doctor or poison control center immediately.

Do not use this product

if seal is broken or missing.

Directions

- Adults and children 2 years of age and older: Apply to affected area not more than 3 to 4 times daily. Children under 2 years of age: consult a doctor.

Other Information

- Keep away from direct sunlight or heat.
- Store at room temperature 15°-30° C (59°-86°F).

Inactive Ingredients

Acrylates/C10-30 Alkyl Acrylate Crosspolymer, Allantoin, Aloe Barbadensis Leaf Juice, Arnica Montana Flower Extract, Boswellia Serrata Resin Extract, Butyrospermum Parkii (Shea) Butter, C13-14 Isoparaffin, Cannabis Sativa Seed Oil, Carbomer, Centella Asiatica Leaf Extract, Cinnamomum Camphora (Camphor) Bark Oil, Dimethicone, Dimethyl Isosorbide, Dipotassium Glycyrrhizate, Disodium EDTA, Emu Oil, Ethoxydiglycol, Eucalyptus Globulus Leaf Oil, Glycerin, Glyceryl Stearate, Helianthus Annuus (Sunflower) Seed Oil, Isopropyl Myristate, Laureth-7, Lavandula Angustifolia (Lavender) Oil, Melaleuca Alternifolia (Tea Tree) Leaf Oil, Methyl Sulfonyl Methane (MSM), PEG-100 Stearate, Phenoxyethanol, Polyacrylamide, Polysorbate 20, Pyridoxine HCL, Sodium Benzoate, Tocopheryl Acetate, Triethanolamine, Water